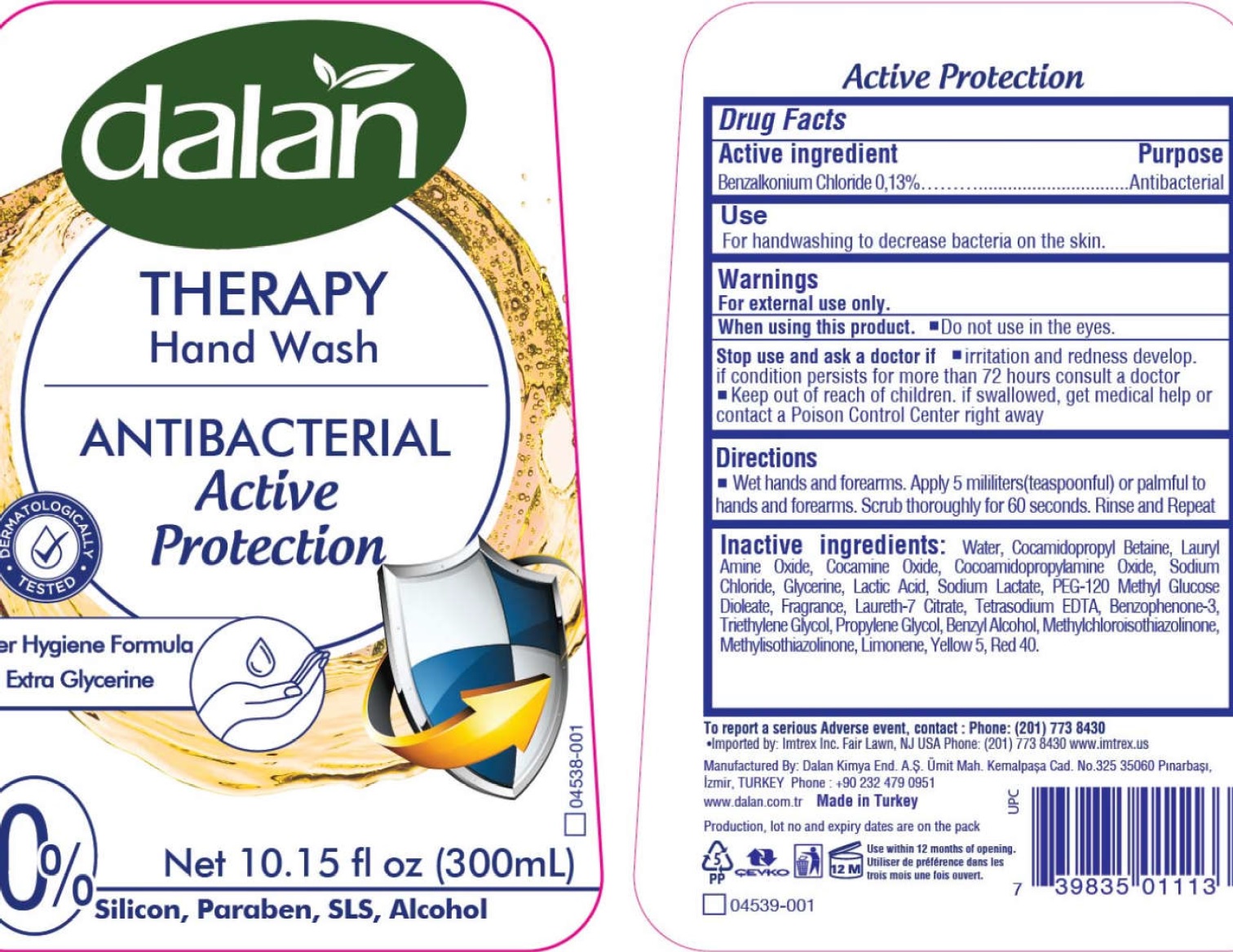 DRUG LABEL: Dalan Therapy Antibacterial Hand Wash, Active Protection
NDC: 51209-014 | Form: LIQUID
Manufacturer: DALAN KIMYA ENDUSTRI ANONIM SIRKETI
Category: otc | Type: HUMAN OTC DRUG LABEL
Date: 20260122

ACTIVE INGREDIENTS: BENZALKONIUM CHLORIDE 1.3 mg/1 mL
INACTIVE INGREDIENTS: WATER; COCAMIDOPROPYL BETAINE; LAURAMINE OXIDE; COCAMINE OXIDE; COCAMIDOPROPYLAMINE OXIDE; SODIUM CHLORIDE; GLYCERIN; LACTIC ACID; SODIUM LACTATE; PEG-120 METHYL GLUCOSE DIOLEATE; EDETATE SODIUM; OXYBENZONE; TRIETHYLENE GLYCOL; PROPYLENE GLYCOL; BENZYL ALCOHOL; METHYLCHLOROISOTHIAZOLINONE; METHYLISOTHIAZOLINONE; LIMONENE, (+)-; FD&C YELLOW NO. 5; FD&C RED NO. 40

Dalan Therapy Antibacterial Hand Wash, Active Protection

Active ingredients

Benzalkonium Chloride 0.13%

Purpose

Antibacterial

Uses

For handwashing to decrease bacteria on the skin.

Warnings

For external use only:

When using this product.

- Do not use in the eyes.

Stop use and ask a doctor if

irritation and redness develop. if condition persists for more than 72 hours consult a doctor

Keep out of reach of children.

If swallowed, get medical help or contact a Poison Control Center right away.

Directions

Wet hands and forearms. Apply 5 milliliters (teaspoonful) or palmful to hands and forearms. Scrub thoroughly for 60 seconds. Rinse and Repeat

Inactive ingredients:

Water, Cocamidopropyl Betaine, Lauryl Amine Oxide, Cocamine Oxide, Cocamidopropylamine Oxide, Sodium Chloride, Glycerine, Lactic Acid, Sodium Lactate, PEG-120 Methyl Glucose Dioleate, Fragrance, Laureth-7 Citrate, Tetrasodium EDTA, Benzophenone-3, Triethylene Glycol, Propylene Glycol, Benzyl Alcohol, Methylchloroisothiazolinone, Methylsothiazolinone, Limonene, Yellow 5, Red 40.